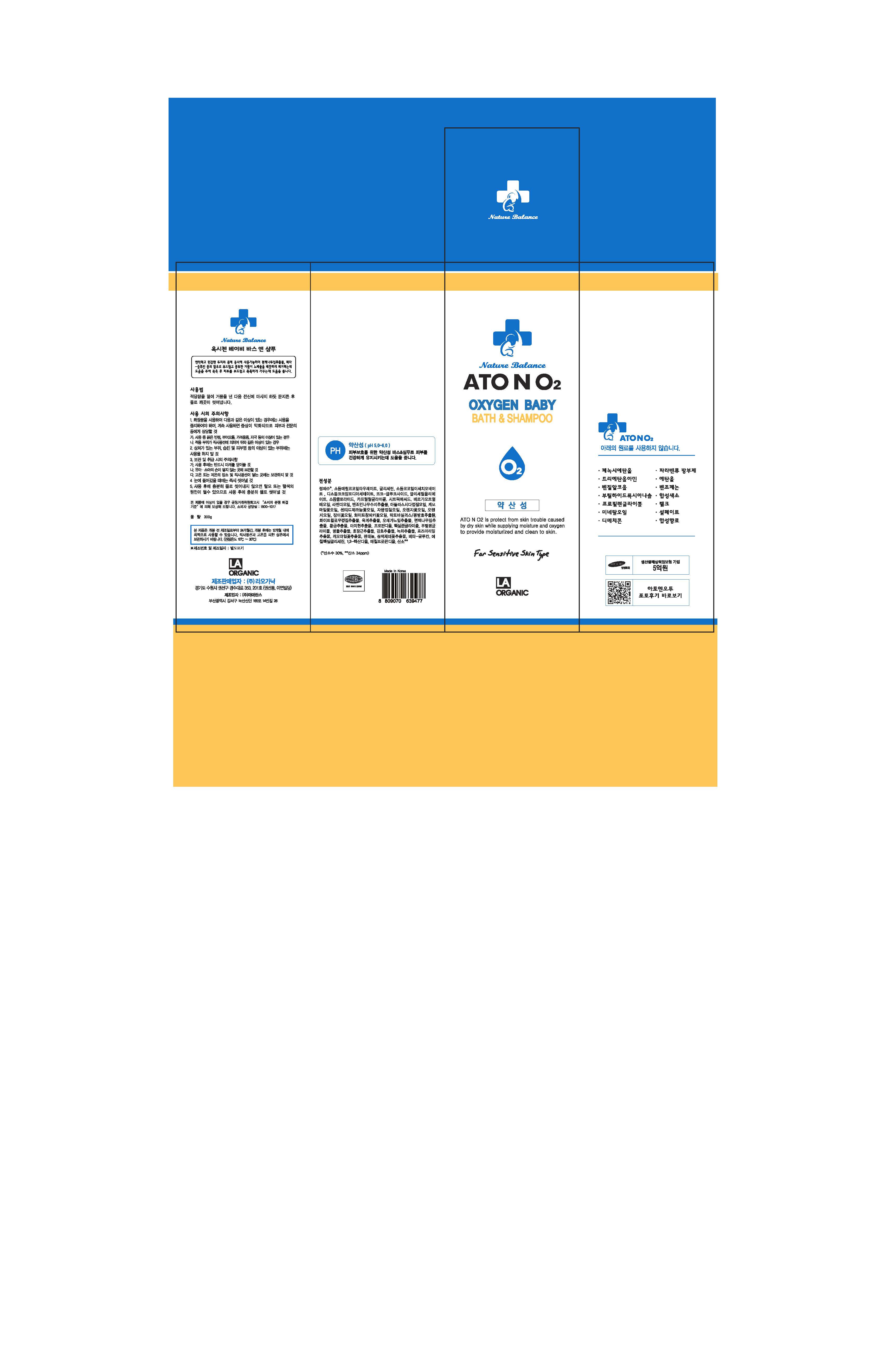 DRUG LABEL: ATONO2 Oxygen Baby Bath and
NDC: 70993-0006 | Form: SHAMPOO
Manufacturer: LAORGANIC Co., Ltd.
Category: otc | Type: HUMAN OTC DRUG LABEL
Date: 20161013

ACTIVE INGREDIENTS: GLYCERIN 3.075 g/100 g
INACTIVE INGREDIENTS: CHAMAECYPARIS OBTUSA LEAF; WATER; SODIUM METHYL COCOYL TAURATE

Drug Facts

ACTIVE INGREDIENT

Glycerin

INACTIVE INGREDIENT

Sodium Methyl Cocoyl Taurate, Sodium Cocoyl Isethionate, Disodium Cocoamphodiacetate, Coco-glucoside, Glyceryl Oleate, Caprylyl Glycol, Chamaecyparis Obtusa Leaf Extract, etc.

PURPOSE

Skin Protectant

keep out of reach of the children

INDICATIONS AND USAGE

Pump an appropriate amount and gently massage the wet facial skin with it. Then rinse with warm water.

WARNINGS

- For external use only
- When using this product

1. If any one of following symptoms occurs when using cosmetics, stop using it and consult a dermatologist.
A. red spot, swelling, itching, stimulus
B. symptoms mentioned above are caused by sunlight.

2. Do not apply on skin where there is wound, eczema, or irritation.

3. Storage and cautions for handling
A. Close stopper after using.
B. Keep out of reach of children.
C. Keep away from high or low temperature and direct sunlight.

4. This is not a medicinal product. Made of 100% cosmetic ingredients, it is a sensitive-skin care product for all skin types.

DOSAGE AND ADMINISTRATION

Take an appropriate amount and work up a lather. Then gently massage onto the whole body and rinse with water.